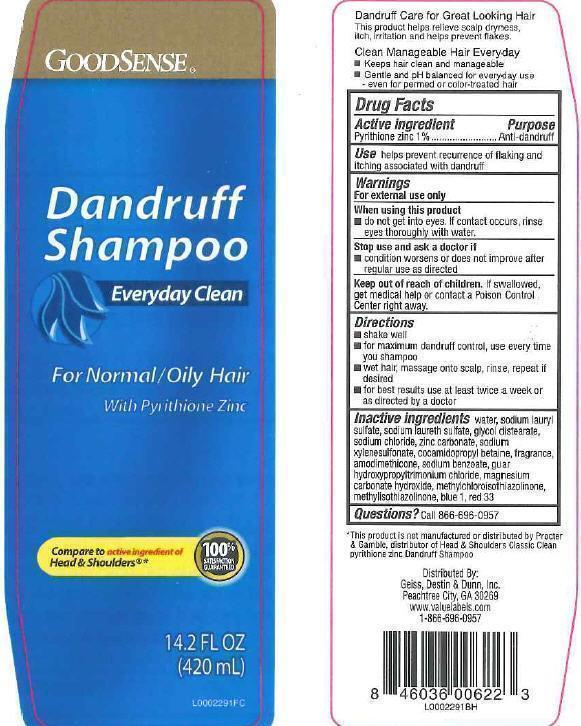 DRUG LABEL: Everyday Clean Dandruff
NDC: 75981-153 | Form: SHAMPOO
Manufacturer: Geiss, Destin + Dunn, Inc
Category: otc | Type: HUMAN OTC DRUG LABEL
Date: 20121026

ACTIVE INGREDIENTS: PYRITHIONE ZINC 1 g/100 mL
INACTIVE INGREDIENTS: WATER; SODIUM LAURYL SULFATE; SODIUM LAURETH SULFATE; GLYCOL DISTEARATE; SODIUM CHLORIDE; ZINC CARBONATE; SODIUM XYLENESULFONATE; COCAMIDOPROPYL BETAINE; AMODIMETHICONE (800 CST); SODIUM BENZOATE; GUAR HYDROXYPROPYLTRIMONIUM CHLORIDE (1.7 SUBSTITUENTS PER SACCHARIDE); MAGNESIUM CARBONATE HYDROXIDE; METHYLCHLOROISOTHIAZOLINONE; METHYLISOTHIAZOLINONE; FD&C BLUE NO. 1; D&C RED NO. 33

Drug Facts

Claims

Dandruff Care for Great Looking Hair

This product helps releive scalp dryness, itch, irritation and helps prevent flakes.

Clean Manageable Hair Everyday

- Keeps hair clean and manageable
- Gentle and pH balanced for everyday use - even for permed or color-treated hair

Active ingredient

Pyrithione zinc 1%

Purpose

Anti-dandruff

Use

Use helps prevent recurrence of flaking and itching associated with dandruff

Warnings

For external use only

When using this product

- do not get into eyes. If contact occurs, rinse eyes thoroughly with water.

Stop use section

Stop use and ask a doctor if

- condition worsens or does not improve after regular use as directed

Keep out of reach of children. If swallowed, get medical help or contact a Poison Control Center right away

Directions

- shake well
- for maximum dandruff control, use everytime you shampoo
- wet hair, massage onto scalp, rinse, repeat if desired
- for best results use at least twice a week or as directed by a doctor

Inactive ingredients

Inactive ingredients water, sodium lauryl sulfate, sodium laureth sulfate, glycol distearate, sodium chloride, zinc carbonate, sodium xylenesulfonate, cocamidopropyl betain , fragrance amodimethicone, sodium benzoate, guar hydroxypropyltrimonium chloride, magnesium carbonate hydroxide, methylchloroisothiazolinone, methylisothiazolinone, blue 1, red 33

Questions

Questions? Call 866-696-0957

Disclaimer

This product is not manufactured or distributed by Procter + Gamble, distributor of Head + Shoulders Classic Clean Pyrithione Zinc Dandruff Shampoo

Adverse Reactions Section

Distributed By:

Geiss, Destin + Dunn, Inc

Peachtree City, GA 30269

www.valuelabels.com

1-866-696-0957

Principal Display Panel

GOODSENSE

Dandruff

Shampoo

Everyday Clean

For Normal/Oily Hair

With Pyrithione Zinc

Compart to acrtive ingredients of Head + Shoulders

14.2 FL OZ

(420 mL)